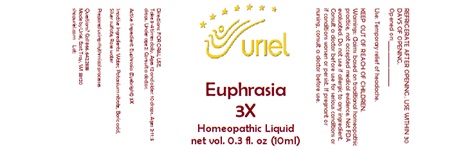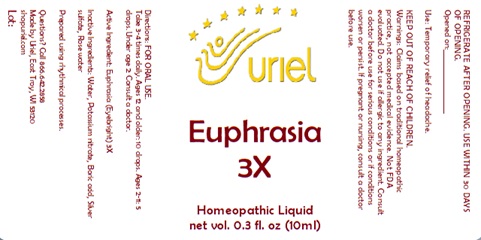 DRUG LABEL: Euphrasia 3X
NDC: 48951-4156 | Form: LIQUID
Manufacturer: Uriel Pharmacy Inc.
Category: homeopathic | Type: HUMAN OTC DRUG LABEL
Date: 20241008

ACTIVE INGREDIENTS: EUPHRASIA STRICTA 3 [hp_X]/1 mL
INACTIVE INGREDIENTS: POTASSIUM NITRATE; WATER; SILVER SULFATE; BORIC ACID; ROSEMARY OIL

Euphrasia 3X

INDICATIONS AND USAGE

Directions: FOR ORAL USE.

DOSAGE AND ADMINISTRATION

Take 3-4 times daily. Ages 12 and older: 10 drops. Ages 2-11: 5 drops. Under age 2: Consult a doctor.

Active Ingredient: Euphrasia (Eyebright) 3X

INACTIVE INGREDIENT

Inactive Ingredients: Water, Potassium nitrate, Boric acid, Silver sulfate, Rose water

Prepared using rhythmical processes

PURPOSE

Use: Temporary relief of headache.

KEEP OUT OF REACH OF CHILDREN.

WARNINGS

Warnings: Claims based on traditional homeopathic practice, not accepted medical evidence. Not FDA evaluated. Do not use if allergic to any ingredient. Consult a doctor before use for serious conditions or if conditions worsen or persist. If pregnant or nursing, consult a doctor before use. Do not use if safety seal is broken or missing.

REFRIGERATE AFTER OPENING. USE WITHIN 30 DAYS OF OPENING.
Opened on:_________________

Questions? Call 866.642.2858
Made by Uriel, East Troy, WI 53120
shopuriel.com Lot: